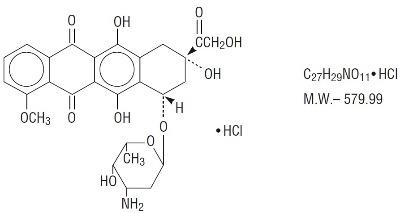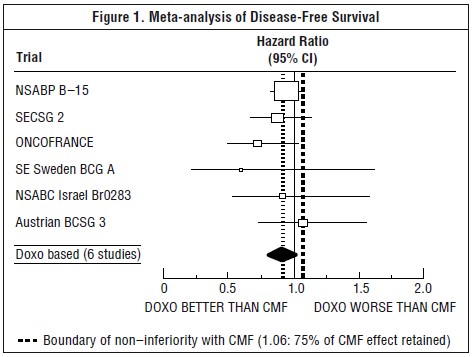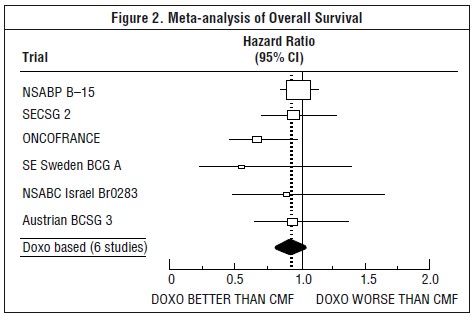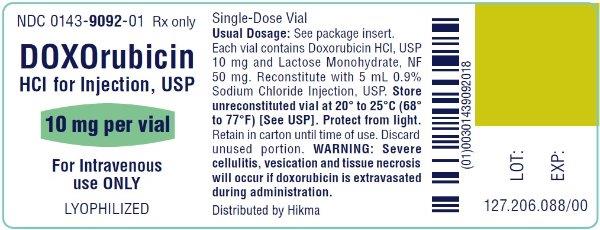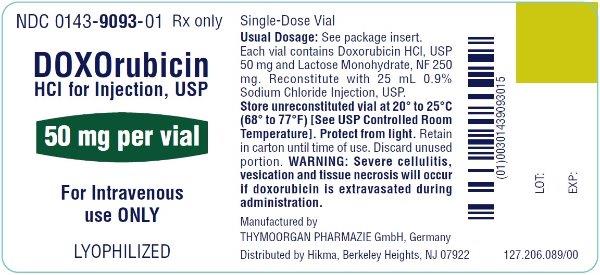 DRUG LABEL: Doxorubicin Hydrochloride
NDC: 0143-9092 | Form: INJECTION, POWDER, LYOPHILIZED, FOR SOLUTION
Manufacturer: Hikma Pharmaceuticals USA Inc.
Category: prescription | Type: HUMAN PRESCRIPTION DRUG LABEL
Date: 20240426

ACTIVE INGREDIENTS: DOXORUBICIN HYDROCHLORIDE 2 mg/1 mL
INACTIVE INGREDIENTS: LACTOSE MONOHYDRATE

HIGHLIGHTS OF PRESCRIBING INFORMATION

These highlights do not include all the information needed to use DOXOrubicin HCl safely and effectively. See full prescribing information for DOXOrubicin HCl.
DOXOrubicin HCl for Injection, USP, for intravenous use
Initial U.S. Approval: 1974

WARNING: CARDIOMYOPATHY, SECONDARY MALIGNANCIES,EXTRAVASATION AND TISSUE NECROSIS, and SEVERE MYELOSUPPRESSION

See full prescribing information for complete boxed warning.

- Cardiomyopathy: Myocardial damage can occur with doxorubicin with incidences from 1% to 20% for cumulative doses from 300 mg/m^2 to 500 mg/m^2 when doxorubicin is administered every 3 weeks. The risk of cardiomyopathy is further increased with concomitant cardiotoxic therapy. Assess left ventricular ejection fraction (LVEF) before and regularly during and after treatment with doxorubicin. (5.1)
- Secondary Malignancies: Secondary acute myelogenous leukemia (AML) and myelodysplastic syndrome (MDS) occur at a higher incidence in patients treated with anthracyclines, including doxorubicin. (5.2)
- Extravasation and Tissue Necrosis: Extravasation of doxorubicin can result in severe local tissue injury and necrosis requiring wide excision and skin grafting. Immediately terminate the drug, and apply ice to the affected area. (5.3)
- Severe myelosuppression resulting in serious infection, septic shock, requirement for transfusions, hospitalization, and death may occur. (5.4)

1 INDICATIONS AND USAGE

Doxorubicin is an anthracycline topoisomerase II inhibitor indicated:

- as a component of multiagent adjuvant chemotherapy for treatment of women with axillary lymph node involvement following resection of primary breast cancer (1.1).
- for the treatment of: acute lymphoblastic leukemia, acute myeloblastic leukemia, Hodgkin lymphoma, Non-Hodgkin lymphoma, metastatic breast cancer, metastatic Wilms’ tumor, metastatic neuroblastoma, metastatic soft tissue sarcoma, metastatic bone sarcomas, metastatic ovarian carcinoma, metastatic transitional cell bladder carcinoma, metastatic thyroid carcinoma, metastatic gastric carcinoma, metastatic bronchogenic carcinoma (1.2).

2 DOSAGE AND ADMINISTRATION

- Single agent: 60 to 75 mg/m^2 given intravenously every 21 days (2.1).
- In combination therapy: 40 to 75 mg/m^2 given intravenously every 21 to 28 days (2.1).
- Discontinue doxorubicin in patients who develop signs or symptoms of cardiomyopathy (2.2).
- Reduce dose in patients with hepatic impairment (2.2).

3 DOSAGE FORMS AND STRENGTHS

- DOXOrubicin HCl for Injection, USP: Vials contain 10 mg and 50 mg as a lyophilized powder (3)

4 CONTRAINDICATIONS

- Severe myocardial insufficiency (4)
- Recent myocardial infarction (4)
- Severe persistent drug-induced myelosuppression (4)
- Severe hepatic impairment (4)
- Hypersensitivity to doxorubicin HCl (4)

5 WARNINGS AND PRECAUTIONS

- Radiation-induced toxicity can be increased by the administration of doxorubicin. Radiation recall can occur in patients who receive doxorubicin after prior radiation therapy (5.7).
- Embryofetal Toxicity: Can cause fetal harm. Advise females of reproductive potential of potential risk to the fetus (5.8).

6 ADVERSE REACTIONS

The most common (>10%) adverse drug reactions are alopecia, nausea and vomiting (6.1).

To report SUSPECTED ADVERSE REACTIONS, contact Hikma Pharmaceuticals USA Inc. at 1-877-845-0689, or FDA at 1-800-FDA-1088 or www.fda.gov/medwatch.

7 DRUG INTERACTIONS

- Avoid concurrent use of doxorubicin with inhibitors and inducers of CYP3A4, CYP2D6, and/or P-gp (7.1).
- Do not administer doxorubicin in combination with trastuzumab due to increased risk of cardiac dysfunction (5.1, 7.2).

8 USE IN SPECIFIC POPULATIONS

- Nursing Mothers: Discontinue drug or nursing taking into consideration importance of drug to mother (8.3).
- Pediatric Use: Recommend long-term follow-up cardiac evaluations due to risk of delayed cardiotoxicity (8.4).
- Females and Males of Reproductive Potential: May impair fertility. Counsel female and male patients on pregnancy planning and prevention (8.6).

FULL PRESCRIBING INFORMATION

WARNING: CARDIOMYOPATHY, SECONDARY MALIGNANCIES,EXTRAVASATION AND TISSUE NECROSIS, and SEVERE MYELOSUPPRESSION

- Cardiomyopathy: Myocardial damage, including acute left ventricular failure can occur with doxorubicin. The risk of cardiomyopathy is proportional to the cumulative exposure with incidences from 1% to 20% for cumulative doses from 300 mg/m^2 to 500 mg/m^2 when doxorubicin is administered every 3 weeks. The risk of cardiomyopathy is further increased with concomitant cardiotoxic therapy. Assess LVEF before and regularly during and after treatment with doxorubicin [see Warnings and Precautions (5.1)].
- Secondary Malignancies: Secondary acute myelogenous leukemia (AML) and myelodysplastic syndrome (MDS) occur at a higher incidence in patients treated with anthracyclines, including doxorubicin [see Warnings and Precautions (5.2)].
- Extravasation and Tissue Necrosis: Extravasation of doxorubicin can result in severe local tissue injury and necrosis requiring wide excision of the affected area and skin grafting. Immediately terminate the drug, and apply ice to the affected area [see Warnings and Precautions (5.3)].
- Severe myelosuppression resulting in serious infection, septic shock, requirement for transfusions, hospitalization, and death may occur [see Warnings and Precautions (5.4)].

1 INDICATIONS AND USAGE

1.1 Adjuvant Breast Cancer

DOXOrubicin HCl for Injection, USP is indicated as a component of multi-agent adjuvant chemotherapy for treatment of women with axillary lymph node involvement following resection of primary breast cancer [see Clinical Studies (14.1)].

1.2 Other Cancers

Doxorubicin is indicated for the treatment of

- acute lymphoblastic leukemia
- acute myeloblastic leukemia
- Hodgkin lymphoma
- non-Hodgkin lymphoma (NHL)
- metastatic breast cancer
- metastatic Wilms’ tumor
- metastatic neuroblastoma
- metastatic soft tissue sarcoma
- metastatic bone sarcoma
- metastatic ovarian carcinoma
- metastatic transitional cell bladder carcinoma
- metastatic thyroid carcinoma
- metastatic gastric carcinoma
- metastatic bronchogenic carcinoma

2 DOSAGE AND ADMINISTRATION

2.1 Recommended Dose

Adjuvant Breast Cancer

The recommended dose of doxorubicin is 60 mg/m^2 administered as an intravenous bolus on day 1 of each 21 day treatment cycle, in combination with cyclophosphamide, for a total of four cycles [see Clinical Studies (14)].

Metastatic Disease, Leukemia, or Lymphoma

- The recommended dose of doxorubicin when used as a single agent is 60 to 75 mg/m^2 intravenously every 21 days.
- The recommended dose of doxorubicin, when administered in combination with other chemotherapy drugs, is 40 to 75 mg/m^2 intravenously every 21 to 28 days.
- Consider use of the lower doxorubicin dose in the recommended dose range or longer intervals between cycles for heavily pretreated patients, elderly patients, or obese patients.
- Cumulative doses above 550 mg/m^2 are associated with an increased risk of cardiomyopathy [see Warnings and Precautions (5.1)].

2.2 Dose Modifications

Cardiac Impairment

Discontinue doxorubicin in patients who develop signs or symptoms of cardiomyopathy.

Hepatic Impairment

Doxorubicin is contraindicated in patients with severe hepatic impairment (Child-Pugh Class C or serum bilirubin >5.0 mg/dL) [see Contraindications (4)].

Decrease the dose of doxorubicin in patients with elevated serum total bilirubin concentrations as follows:

Serum bilirubin concentration | Doxorubicin Dose reduction
1.2 to 3 mg/dL | 50 %
3.1 to 5 mg/dL | 75 %
greater than 5 mg/dL | Do not initiate doxorubicin; Discontinue doxorubicin

[see Warnings and Precautions (5.5) and Use in Specific Population (8.7)]

2.3 Preparation and Administration

Preparation of DOXOrubicin HCl for Injection, USP;

Reconstitute doxorubicin hydrochloride for injection with 0.9% Sodium Chloride Injection to obtain a final concentration of 2 mg per mL as follows:

- 5 mL 0.9% Sodium Chloride Injection to reconstitute 10 mg doxorubicin HCl vial
- 25 mL 0.9% Sodium Chloride Injection to reconstitute 50 mg doxorubicin HCl vial

Gently shake vial until the contents have dissolved.

Protect reconstituted solution from light.

Administration

Visually inspect parenteral drug products for particulate matter and discoloration prior to administration, whenever solution and container permit. Discard if the solution is discolored, cloudy, or contains particulate matter.

Storage of vials of DOXOrubicin HCl for Injection, USP following reconstitution under refrigerated conditions can result in the formation of a gelled product. Place gelled product at room temperature [15º to 30ºC (59º to 86ºF)] for 2 to 4 hours to return the product to a slightly viscous, mobile solution.

Administration by Intravenous Injection:

- Administer doxorubicin as an intravenous injection through a central intravenous line or a secure and free-flowing peripheral venous line containing 0.9% Sodium Chloride Injection, 0.45% Sodium Chloride Injection, or 5% Dextrose Injection.
- Administer doxorubicin intravenously over 3 to 10 minutes. Decrease the rate of doxorubicin administration if erythematous streaking along the vein proximal to the site of infusion or facial flushing occur.

Administration by Continuous Intravenous Infusion:

- Infuse only through a central catheter. Decrease the rate of doxorubicin administration if erythematous streaking along the vein proximal to the site of infusion or facial flushing occur.
- Protect from light from preparation for infusion until completion of infusion.

Management of Suspected Extravasation

Discontinue doxorubicin for burning or stinging sensation or other evidence indicating perivenous infiltration or extravasation. Manage confirmed or suspected extravasation as follows:

- Do not remove the needle until attempts are made to aspirate extravasated fluid.
- Do not flush the line.
- Avoid applying pressure to the site.
- Apply ice to the site intermittently for 15 min 4 times a day for 3 days.
- If the extravasation is in an extremity, elevate the extremity.
- In adults, consider administration of dexrazoxane [see Warnings and Precautions (5.3)].

Incompatibility with Other Drugs

Do not admix doxorubicin with other drugs. If doxorubicin is mixed with heparin or fluorouracil a precipitate may form. Avoid contact with alkaline solutions which can lead to hydrolysis of doxorubicin.

2.4 Procedures for Proper Handling and Disposal

Handle and dispose of doxorubicin consistent with recommendations for the handling and disposal of hazardous drugs.^1

Treat accidental contact with the skin or eyes immediately by copious lavage with water, or soap and water, or sodium bicarbonate solution. Do not abrade the skin by using a scrub brush. Seek medical attention.

3 DOSAGE FORMS AND STRENGTHS

DOXOrubicin HCl for Injection, USP: Vials contain 10 mg and 50 mg doxorubicin hydrochloride as a red-orange lyophilized powder.

4 CONTRAINDICATIONS

Doxorubicin is contraindicated in patients with:

- Severe myocardial insufficiency [see Warnings and Precautions (5.1)]
- Recent (occurring within the past 4 to 6 weeks) myocardial infarction [see Warnings and Precautions (5.1)]
- Severe persistent drug-induced myelosuppression [see Warnings and Precautions (5.4)]
- Severe hepatic impairment (defined as Child Pugh Class C or serum bilirubin level greater than 5 mg/dL) [see Warnings and Precautions (5.5)]
- Severe hypersensitivity reaction to doxorubicin including anaphylaxis [see Adverse Reactions (6.2)]

5 WARNINGS AND PRECAUTIONS

5.1 Cardiomyopathy and Arrhythmias

Cardiomyopathy

Doxorubicin can result in myocardial damage, including acute left ventricular failure. The risk of cardiomyopathy is generally proportional to the cumulative exposure. Include prior doses of other anthracyclines or anthracenediones in calculations of total cumulative dosage for doxorubicin. Cardiomyopathy may develop during treatment or up to several years after completion of treatment and can include decrease in LVEF and signs and symptoms of congestive heart failure (CHF). The probability of developing cardiomyopathy is estimated to be 1 to 2% at a total cumulative dose of 300 mg/m^2 of doxorubicin, 3 to 5% at a dose of 400 mg/m^2, 5 to 8% at a dose of 450 mg/m^2, and 6 to 20% at a dose of 500 mg/m^2, when doxorubicin is administered every 3 weeks. There is an additive or potentially synergistic increase in the risk of cardiomyopathy in patients who have received radiotherapy to the mediastinum or concomitant therapy with other known cardiotoxic agents such as cyclophosphamide and trastuzumab.

Pericarditis and myocarditis have also been reported during or following doxorubicin treatment.

Assess left ventricular cardiac function (e.g., MUGA or echocardiogram) prior to initiation of doxorubicin, during treatment to detect acute changes, and after treatment to detect delayed cardiotoxicity. Increase the frequency of assessments as the cumulative dose exceeds 300 mg/m^2 . Use the same method of assessment of LVEF at all time points [see Use in Specific Populations (8.4)].

Consider the use of dexrazoxane to reduce the incidence and severity of cardiomyopathy due to doxorubicin administration in patients who have received a cumulative doxorubicin dose of 300 mg/m^2 and who will continue to receive doxorubicin.

Arrhythmias

Doxorubicin can result in arrhythmias, including life-threatening arrhythmias, during or within a few hours after doxorubicin administration and at any time point during treatment. Tachyarrhythmias, including sinus tachycardia, premature ventricular contractions, and ventricular tachycardia, as well as bradycardia may occur. Electrocardiographic changes including non-specific ST-T wave changes, atrioventricular and bundle-branch block can also occur. These electrocardiographic changes may be transient and self-limited and may not require dose-modifications of doxorubicin.

5.2 Secondary Malignancies

The risk of developing secondary acute myelogenous leukemia (AML) and myelodysplastic syndrome (MDS) is increased following treatment with doxorubicin. Cumulative incidences ranged from 0.2% at five years to 1.5% at 10 years in two separate trials involving the adjuvant treatment of women with breast cancer. These leukemias generally occur within 1 to 3 years of treatment.

5.3 Extravasation and Tissue Necrosis

Extravasation of doxorubicin can result in severe local tissue injury manifesting as blistering, ulceration, and necrosis requiring wide excision of the affected area and skin grafting. When given via a peripheral venous line, infuse doxorubicin over 10 minutes or less to minimize the risk of thrombosis or perivenous extravasation. If signs or symptoms of extravasation occur, immediately terminate the injection or infusion [see Dosage and Administration (2.3)]. Extravasation may be present in patients who do not experience a stinging or burning sensation or when blood return is present on aspiration of the infusion needle. If extravasation is suspected, apply ice to the site intermittently for 15 minutes, 4 times a day for 3 days. If appropriate, administer dexrazoxane at the site of extravasation as soon as possible and within the first 6 hours after extravasation.

5.4 Severe Myelosuppression

Doxorubicin can cause myelosuppression. In Study 1, the incidence of severe myelosuppression was: grade 4 leukopenia (0.3%), grade 3 leukopenia (3%), and grade 4 thrombocytopenia (0.1%). A dose-dependent, reversible neutropenia is the predominant manifestation of hematologic toxicity from doxorubicin. When doxorubicin is administered every 21 days, the neutrophil count reaches its nadir 10 to 14 days after administration with recovery usually occurring by the 21st day.

Obtain baseline assessment of blood counts and carefully monitor patients during treatment for possible clinical complications due to myelosuppression.

5.5 Use in Patients with Hepatic Impairment

The clearance of doxorubicin is decreased in patients with elevated serum bilirubin with an increased risk of toxicity [see Use in Specific Populations (8.7) and Clinical Pharmacology (12.3)]. Reduce the dose of doxorubicin in patients with serum bilirubin levels of 1.2 to 5.0 mg/dL [see Dosage and Administration (2.2)]. Doxorubicin is contraindicated in patients with severe hepatic impairment (defined as Child Pugh Class C or serum bilirubin level greater than 5 mg/dL) [see Contraindications (4)]. Obtain liver tests including SGOT, SGPT, alkaline phosphatase, and bilirubin prior to and during doxorubicin therapy.

5.6 Tumor Lysis Syndrome

Doxorubicin may induce tumor lysis syndrome in patients with rapidly growing tumors. Evaluate blood uric acid levels, potassium, calcium, phosphate, and creatinine after initial treatment. Hydration, urine alkalinization, and prophylaxis with allopurinol to prevent hyperuricemia may minimize potential complications of tumor lysis syndrome.

5.7 Radiation Sensitization and Radiation Recall

Doxorubicin can increase radiation-induced toxicity to the myocardium, mucosa, skin, and liver. Radiation recall, including but not limited to cutaneous and pulmonary toxicity, can occur in patients who receive doxorubicin after prior radiation therapy.

5.8 Embryofetal Toxicity

Doxorubicin can cause fetal harm when administered to a pregnant woman. Doxorubicin was teratogenic and embryotoxic in rats and rabbits at doses lower than the recommended human dose.

If this drug is used during pregnancy, or if the patient becomes pregnant while taking this drug, apprise the patient of the potential hazard to a fetus [see Use in Specific Populations (8.1)].

Advise female patients of reproductive potential to use highly effective contraception during treatment with doxorubicin and for 6 months after treatment. Advise patients to contact their healthcare provider if they become pregnant, or if pregnancy is suspected, while taking doxorubicin [see Use in Specific Populations (8.1) and (8.6)].

6 ADVERSE REACTIONS

The following adverse reactions are discussed in more detail in other sections of the labeling.

- Cardiomyopathy and Arrhythmias [see Warnings and Precautions (5.1)]
- Secondary Malignancies [see Warnings and Precautions (5.2)]
- Extravasation and Tissue Necrosis [see Warnings and Precautions (5.3)]
- Severe Myelosuppression [see Warnings and Precautions (5.4)]
- Tumor Lysis Syndrome [see Warnings and Precautions (5.6)]
- Radiation Sensitization and Radiation Recall [see Warnings and Precautions (5.7)]

6.1 Clinical Trial Experience in Breast Cancer

Because clinical trials are conducted under widely varying conditions, adverse reaction rates observed in the clinical trials of a drug cannot be directly compared to rates in the clinical trials of another drug and may not reflect the rates observed in clinical practice.

The safety data below were collected from 1492 women who received doxorubicin at a dose of 60 mg/m^2 and cyclophosphamide at a dose of 600 mg/m^2 (AC) every 3 weeks for 4 cycles for the adjuvant treatment of axillary lymph node positive breast cancer. The median number of cycles received was 4. Selected adverse reactions reported in this study are provided in Table 1. No treatment-related deaths were reported in patients on either arm of the study.

Table 1. Selected Adverse Reactions in Patients with Early Breast Cancer Involving Axillary Lymph Nodes
Adverse reactions, % of patients | AC*; N=1492 | Conventional CMF; N=739
Leukopenia; Grade 3 (1,000 to 1,999 /mm^3); Grade 4 (<1000 /mm^3) | 3.4; 0.3 | 9.4; 0.3
Thrombocytopenia; Grade 3 (25,000 to 49,999 /mm^3); Grade 4 (<25,000 /mm^3) | 0; 0.1 | 3.0; 0
Shock, sepsis | 2 | 1
Systemic infection | 2 | 1
Vomiting; Vomiting ≤12 hours; Vomiting >12 hours; Intractable | 34; 37; 5 | 25; 12; 2
Alopecia | 92 | 71
Cardiac dysfunction; Asymptomatic; Transient; Symptomatic | 0.2; 0.1; 0.1 | 0.1; 0; 0

* Includes pooled data from patients who received either AC alone for 4 cycles, or who were treated with AC for 4 cycles followed by 3 cycles of CMF

6.2 Postmarketing Experience

The following adverse reactions have been identified during post-approval use of doxorubicin. Because these reactions are reported voluntarily from a population of uncertain size, it is not always possible to reliably estimate their frequency or establish a causal relationship to drug exposure.

Cardiac – cardiogenic shock

Cutaneous – Skin and nail hyperpigmentation, oncolysis, rash, itching, photosensitivity, urticaria, acral erythema, palmar plantar erythrodysesthesia

Gastrointestinal – Nausea, mucositis, stomatitis, necrotizing colitis, typhlitis, gastric erosions, gastrointestinal tract bleeding, hematochezia, esophagitis, anorexia, abdominal pain, dehydration, diarrhea, hyperpigmentation of the oral mucosa

Hypersensitivity – Anaphylaxis

Laboratory Abnormalities –Increased alanine aminotransferase, increased aspartate aminotransferase

Neurological – Peripheral sensory and motor neuropathy, seizures, coma

Ocular – Conjunctivitis, keratitis, lacrimation

Vascular – Phlebosclerosis, phlebitis/thrombophlebitis, hot flashes, thromboembolism

Other – Malaise/asthenia, fever, chills, weight gain

7 DRUG INTERACTIONS

7.1 Effect of CYP3A4 Inhibitors, Inducers and P-gp

Doxorubicin is a major substrate of cytochrome P450 CYP3A4 and CYP2D6, and P-glycoprotein (P-gp). Clinically significant interactions have been reported with inhibitors of CYP3A4, CYP2D6, and/or P-gp (e.g., verapamil), resulting in increased concentration and clinical effect of doxorubicin. Inducers of CYP3A4 (e.g., phenobarbital, phenytoin, St. John’s Wort) and P-gp inducers may decrease the concentration of doxorubicin. Avoid concurrent use of doxorubicin with inhibitors and inducers of CYP3A4, CYP2D6, or P-gp.

7.2 Trastuzumab

Concurrent use of trastuzumab and doxorubicin results in an increased risk of cardiac dysfunction. Avoid concurrent administration of doxorubicin and trastuzumab. The appropriate interval for administering doxorubicin following trastuzumab therapy has not been determined [see Warnings and Precautions (5.1)].

7.3 Paclitaxel

Paclitaxel, when given prior to doxorubicin, increases the plasma-concentrations of doxorubicin and its metabolites. Administer doxorubicin prior to paclitaxel if used concomitantly.

7.4 Dexrazoxane

Do not administer dexrazoxane as a cardioprotectant at the initiation of doxorubicin containing chemotherapy regimens. In a randomized trial in women with metastatic breast cancer, initiation of dexrazoxane with doxorubicin based chemotherapy resulted in a significantly lower tumor response rate (48% vs. 63%; p=0.007) and shorter time to progression than in women who received doxorubicin based chemotherapy alone.

7.5 6-Mercaptopurine

Doxorubicin may potentiate 6-mercaptopurine-induced hepatotoxicity. In 11 patients with refractory leukemia treated with 6-mercaptopurine (500 mg/m^2 intravenously daily for 5 days per cycle every 2 to 3 weeks) and doxorubicin (50 mg/m^2 intravenous once per cycle every 2 to 3 weeks) alone or with vincristine and prednisone, all developed hepatic dysfunction manifested by elevations of total serum bilirubin, alkaline phosphatase and aspartate aminotransferase.

8 USE IN SPECIFIC POPULATIONS

8.1 Pregnancy

Pregnancy Category D

Risk Summary

Doxorubicin can cause fetal harm when administered to a pregnant woman. Doxorubicin was teratogenic and embryotoxic in rats and rabbits at doses approximately 0.07 times (based on body surface area) the recommended human dose of 60 mg/m^2 . If this drug is used during pregnancy, or if the patient becomes pregnant while taking this drug, apprise the patient of the potential hazard to a fetus.

Animal Data

Doxorubicin was teratogenic and embryotoxic at doses of 0.8 mg/kg/day (about 0.07 times the recommended human dose based on body surface area) when administered during the period of organogenesis in rats. Teratogenicity and embryotoxicity were also seen using discrete periods of treatment. The most susceptible was the 6- to 9-day gestation period at doses of 1.25 mg/kg/day and greater. Characteristic malformations included esophageal and intestinal atresia, tracheo-esophageal fistula, hypoplasia of the urinary bladder, and cardiovascular anomalies. Doxorubicin was embryotoxic (increase in embryofetal deaths) and abortifacient at 0.4 mg/kg/day (about 0.07 times the recommended human dose based on body surface area) in rabbits when administered during the period of organogenesis.

8.3 Nursing Mothers

Doxorubicin has been detected in the milk of at least one lactating patient [see Clinical Pharmacology (12.3)]. Because of the potential for serious adverse reactions in nursing infants from doxorubicin , a decision should be made whether to discontinue nursing or discontinue the drug, taking into account the importance of the drug to the mother.

8.4 Pediatric Use

Based on postmarketing reports, pediatric patients treated with doxorubicin are at risk for developing late cardiovascular dysfunction. Risk factors include young age at treatment (especially < 5 years), high cumulative doses and receipt of combined modality therapy. Long-term periodic cardiovascular monitoring is recommended for all pediatric patients who have received doxorubicin. Doxorubicin, as a component of intensive chemotherapy regimens administered to pediatric patients, may contribute to prepubertal growth failure and may also contribute to gonadal impairment, which is usually temporary.

There are no recommended dose adjustments based on age. Doxorubicin clearance was increased in patients aged 2 years to 20 years as compared to adults, while doxorubicin clearance was similar in children less than 2 years as compared to adults [see Clinical Pharmacology (12.3)].

8.5 Geriatric Use

Clinical experience in patients who were 65 years of age and older who received doxorubicin based chemotherapy regimens for metastatic breast cancer showed no overall differences in safety and effectiveness compared with younger patients.

8.6 Females and Males of Reproductive Potential

Contraception

Females

Doxorubicin can cause fetal harm when administered during pregnancy. Advise female patients of reproductive potential to use highly effective contraception during treatment with doxorubicin and for 6 months after treatment. Advise patients to contact their healthcare provider if they become pregnant, or if pregnancy is suspected, while taking doxorubicin [see Use in Specific Populations (8.1)].

Males

Doxorubicin may damage spermatozoa and testicular tissue, resulting in possible genetic fetal abnormalities. Males with female sexual partners of reproductive potential should use effective contraception during and for 6 months after treatment [see Nonclinical Toxicology (13.1)].

Infertility

Females

In females of reproductive potential, doxorubicin may cause infertility and result in amenorrhea. Premature menopause can occur. Recovery of menses and ovulation is related to age at treatment [see Nonclinical Toxicology (13.1)].

Males

Doxorubicin may result in oligospermia, azoospermia, and permanent loss of fertility. Sperm counts have been reported to return to normal levels in some men. This may occur several years after the end of therapy.

8.7 Hepatic Impairment

The clearance of doxorubicin was reduced in patients with elevated serum bilirubin levels. Reduce the dose of doxorubicin in patients with serum bilirubin levels greater than 1.2 mg/dL [see Dosage and Administration (2.2) and Warnings and Precautions (5.5)].

Doxorubicin is contraindicated in patients with severe hepatic impairment (defined as Child Pugh Class C or serum bilirubin levels greater than 5 mg/dL) [see Contraindications (4)].

10 OVERDOSAGE

Few cases of overdose have been described. A 58-year-old man with acute lymphoblastic leukemia received 10-fold overdose of doxorubicin (300 mg/m^2) in one day. He was treated with charcoal filtration, hemopoietic growth factor (G-CSF), proton pump inhibitor and antimicrobial prophylaxis. The patient suffered sinus tachycardia, grade 4 neutropenia and thrombocytopenia for 11 days, severe mucositis and sepsis. The patient recovered completely 26 days after the overdose. A 17-year-old girl with osteogenic sarcoma received 150 mg of doxorubicin daily for 2 days (intended dose was 50 mg per day for 3 days). The patient developed severe mucositis on days 4 to 7 after the overdose and chills and pyrexia on day 7. The patient was treated with antibiotics and platelets and recovered 18 days after overdose.

11 DESCRIPTION

Doxorubicin is a cytotoxic anthracycline antibiotic isolated from cultures of Streptomyces peucetius var.caesius. Doxorubicin consists of a naphthacenequinone nucleus linked through a glycosidic bond at ring atom 7 to an amino sugar, daunosamine. Chemically, doxorubicin hydrochloride is (8S,10S)-10-[(3-Amino-2,3,6-trideoxy-a-L-lyxo-hexopyranosyl)-oxy]-8-glycoloyl-7,8,9,10-tetrahydro-6,8,11-trihydroxy-1-methoxy-5,12-naphthacenedione hydrochloride. The structural formula is as follows:

Doxorubicin binds to nucleic acids, presumably by specific intercalation of the planar anthracycline nucleus with the DNA double helix. The anthracycline ring is lipophilic, but the saturated end of the ring system contains abundant hydroxyl groups adjacent to the amino sugar, producing a hydrophilic center. The molecule is amphoteric, containing acidic functions in the ring phenolic groups and a basic function in the sugar amino group. It binds to cell membranes as well as plasma proteins.

It is supplied in the hydrochloride form as a sterile red-orange lyophilized powder containing lactose for intravenous use only.

DOXOrubicin HCl for Injection, USP:

Each 10 mg lyophilized vial contains 10 mg of Doxorubicin Hydrochloride, USP and 50 mg of Lactose Monohydrate, NF.

Each 50 mg lyophilized vial contains 50 mg of Doxorubicin Hydrochloride, USP and 250 mg of Lactose Monohydrate, NF.

12 CLINICAL PHARMACOLOGY

12.1 Mechanism of Action

The cytotoxic effect of doxorubicin on malignant cells and its toxic effects on various organs are thought to be related to nucleotide base intercalation and cell membrane lipid binding activities of doxorubicin. Intercalation inhibits nucleotide replication and action of DNA and RNA polymerases. The interaction of doxorubicin with topoisomerase II to form DNA-cleavable complexes appears to be an important mechanism of doxorubicin cytocidal activity.

12.3 Pharmacokinetics

Pharmacokinetic studies conducted in patients with various types of tumors have shown that doxorubicin follows multiphasic disposition after intravenous injection. The distribution half-life is approximately 5 minutes, while the terminal half-life is 20 to 48 hours. In four patients, doxorubicin demonstrated dose-independent pharmacokinetics across a dose range of 30 to 70 mg/m^2 .

Distribution

Steady-state distribution volume ranges from 809 to 1214 L/m^2. Binding of doxorubicin and its major metabolite, doxorubicinol, to plasma proteins is about 75% and is independent of plasma concentration of doxorubicin up to 1.1 mcg/mL.

Doxorubicin was measured in the milk of one lactating patient after therapy with 70 mg/m^2 of doxorubicin given as a 15 minute intravenous infusion. The peak milk concentration at 24 hours after treatment was 4.4 fold greater than the corresponding plasma concentration. Doxorubicin was detectable in the milk up to 72 hours.

Doxorubicin does not cross the blood brain barrier.

Metabolism

Enzymatic reduction at the 7 position and cleavage of the daunosamine sugar yields aglycones which are accompanied by free radical formation, the local production of which may contribute to the cardiotoxic activity of doxorubicin. Disposition of doxorubicinol in patients is formation rate limited, with the terminal half-life of doxorubicinol being similar to doxorubicin. The relative exposure of doxorubicinol, i.e., the ratio between the AUC of doxorubicinol and the AUC of doxorubicin is approximately 0.5.

Excretion

Plasma clearance is in the range 324 to 809 mL/min/m^2 and is predominately by metabolism and biliary excretion. Approximately 40% of the dose appears in the bile in 5 days, while only 5 to 12% of the drug and its metabolites appear in the urine during the same time period. In urine, <3% of the dose was recovered as doxorubicinol over 7 days.

Systemic clearance of doxorubicin is significantly reduced in obese women with ideal body weight greater than 130%. There was a significant reduction in clearance without any change in volume of distribution in obese patients when compared with normal patients with less than 115% ideal body weight.

Pediatric patients

Following administration of doses ranging from 10 to 75 mg/m^2 of doxorubicin to 60 children and adolescents ranging from 2 months to 20 years of age, doxorubicin clearance averaged 1443 ± 114 mL/min/m^2. Further analysis demonstrated that clearance in 52 children greater than 2 years of age (1540 mL/min/m^2) was increased compared with adults. However, clearance in infants younger than 2 years of age (813 mL/min/m^2) was decreased compared with older children and approached the range of clearance values determined in adults [see Use in Specific Populations (8.4)].

Patient Gender

There is no recommended dose adjustment based on gender. A published clinical study involving 6 men and 21 women with no prior anthracycline therapy reported a significantly higher median doxorubicin clearance in men compared to women (1088 mL/min/m^2 versus 433 mL/min/m^2). However, the terminal half-life of doxorubicin was longer in men compared to women (54 versus 35 hours).

Patients with hepatic impairment

The clearance of doxorubicin and doxorubicinol was reduced in patients with elevation in serum bilirubin [see Dosage and Administration (2.2) and Warnings and Precautions (5.5)].

13 NONCLINICAL TOXICOLOGY

13.1 Carcinogenesis, Mutagenesis, Impairment of Fertility

Doxorubicin treatment results in an increased risk of secondary malignancies based on postmarketing reports [see Warnings and Precautions (5.2)]. Doxorubicin was mutagenic in the in vitro Ames assay, and clastogenic in multiple in vitro assays (CHO cell, V79 hamster cell, human lymphoblast, and SCE assays) and the in vivo mouse micronucleus assay.

Doxorubicin decreased fertility in female rats at the doses of 0.05 and 0.2 mg/kg/day (approximately 0.005 and 0.02 times the recommended human dose, based on body surface area)

A single intravenous dose of 0.1 mg/kg doxorubicin (approximately 0.01 times the recommended human dose based on body surface area) was toxic to male reproductive organs in animal studies, producing testicular atrophy, diffuse degeneration of the seminiferous tubules, and oligospermia/hypospermia in rats. Doxorubicin induces DNA damage in rabbit spermatozoa and dominant lethal mutations in mice.

14 CLINICAL STUDIES

The clinical efficacy of doxorubicin containing regimens for the post-operative, adjuvant treatment of surgically resected breast cancer was evaluated in a meta-analysis conducted by the Early Breast Cancer Trialists Collaborative Group (EBCTCG). The EBCTCG meta-analyses compared cyclophosphamide, methotrexate, and 5-fluorouracil (CMF) to no chemotherapy (19 trials including 7523 patients) and doxorubicin containing regimens with CMF as an active control (6 trials including 3510 patients). Data from the meta-analysis of trials comparing CMF to no therapy were used to establish the historical treatment effect size for CMF regimens. The major efficacy outcome measures were disease-free survival (DFS) and overall survival (OS).

Of the 3510 women (2157 received doxorubicin containing regimens and 1353 received CMF treatment) with early breast cancer involving axillary lymph nodes included in the six trials from the meta-analyses, approximately 70% were premenopausal and 30% were postmenopausal. At the time of the meta-analysis, 1745 first recurrences and 1348 deaths had occurred. The analyses demonstrated that doxorubicin containing regimens retained at least 75% of the historical CMF adjuvant effect on DFS with a hazard ratio (HR) of 0.91 (95% CI, 0.82 to 1.01) and on OS with a HR of 0.91 (95% CI, 0.81 to 1.03). Results of these analyses for both DFS and OS are provided in Table 2 and Figures 1 and 2.

Table 2. Summary of Randomized Trials Comparing Doxorubicin Containing Regimens Versus CMF in Meta-Analysis

Study (starting year) | Regimens | No. of Cycles | No. of Patients | Doxorubicin Containing Regimens vs. CMF HR** (95% CI)
Study (starting year) | Regimens | No. of Cycles | No. of Patients | DFS | OS

NSABP B-15 (1984) | AC; CMF | 4; 6 | 1562*; 776 | 0.93 (0.82 to 1.06) | 0.97 (0.83 to 1.12)
SECSG 2 (1976) | FAC; CMF | 6; 6 | 260; 268 | 0.86 (0.66 to 1.13) | 0.93 (0.69 to 1.26)
ONCOFRANCE (1978) | FACV; CMF | 12; 12 | 138; 113 | 0.71 (0.49 to 1.03) | 0.65 (0.44 to 0.96)
SE Sweden BCG A (1980) | AC; CMF | 6; 6 | 21; 22 | 0.59 (0.22 to 1.61) | 0.53 (0.21 to 1.37)
NSABC Israel Br0283 (1983) | AVbCMF†; CMF | 4; 6; 6 | 55; 50 | 0.91 (0.53 to 1.57) | 0.88 (0.47 to 1.63)
Austrian BCSG 3 (1984) | CMFVA; CMF | 6; 8 | 121; 124 | 1.07 (0.73 to 1.55) | 0.93 (0.64 to 1.35)
Combined Studies | Doxorubicin Containing Regimens CMF |  | 2157; 1353 | 0.91 (0.82 to 1.01) | 0.91 (0.81 to 1.03)

Abbreviations: DFS = disease free survival; OS = overall survival; AC = doxorubicin, cyclophosphamide; AVbCMF = doxorubicin, vinblastine, cyclophosphamide, methotrexate, 5-fluorouracil; CMF = cyclophosphamide, methotrexate, 5-fluorouracil; CMFVA = cyclophosphamide, methotrexate, 5-fluorouracil, vincristine, doxorubicin; FAC = 5-fluorouracil, doxorubicin, cyclophosphamide; FACV = 5-fluorouracil, doxorubicin, cyclophosphamide, vincristine; HR = hazard ratio; CI = confidence interval

* Includes pooled data from patients who received either AC alone for 4 cycles, or who were treated with AC for 4
cycles followed by 3 cycles of CMF.
** A hazard ratio of less than 1 indicates that the treatment with doxorubicin containing regimens is associated
with lower risk of disease recurrences or death compared to the treatment with CMF.

† Patients received alternating cycles of AVb and CMF.

15 REFERENCES

1. “Hazardous Drugs”. OSHA. http://www.osha.gov/SLTC/hazardousdrugs/index.html

16 HOW SUPPLIED/STORAGE AND HANDLING

DOXOrubicin HCI for Injection, USP is supplied as a sterile red-orange lyophilized powder in single dose flip-top vials in the following package strengths:

NDC 0143-9092-01: 10 mg vial; individually boxed.

NDC 0143-9093-01: 50 mg vial; individually boxed.

Store all vials at 20° to 25°C (68° to 77°F) [See USP Controlled Room Temperature]. Protect from light. Retain in carton until time of use. Discard unused portion.

Reconstituted Solution Stability

After adding the diluent, the vial should be shaken and the contents allowed to dissolve. The reconstituted solution is stable for 7 days at room temperature and under normal room light (100 foot-candles) and 15 days under refrigeration (2° to 8°C). It should be protected from exposure to sunlight. Discard any unused solution from the 10 mg and 50 mg single dose vials.

Handling and Disposal

Handle and dispose of DOXOrubicin HCl for Injection, USP consistent with recommendations for the handling and disposal of hazardous drugs.^1

17 PATIENT COUNSELING INFORMATION

See FDA-Approved Patient Labeling (Patient Information). Inform patients of the following:

- Doxorubicin can cause irreversible myocardial damage. Advise patients to contact a healthcare provider for symptoms of heart failure during or after treatment with doxorubicin [see Warnings and Precautions (5.1)].
- There is an increased risk of treatment-related leukemia from doxorubicin [see Warnings and Precautions (5.2)].
- Doxorubicin can reduce the absolute neutrophil count resulting in an increased risk of infection. Advise patients to contact a healthcare provider for new onset fever or symptoms of infection [see Warnings and Precautions (5.4)].
- Doxorubicin can cause fetal harm when administered during pregnancy. Advise females of reproductive potential to use effective contraception during treatment with doxorubicin and for 6 months after treatment, and to contact their healthcare provider if they become pregnant, or if pregnancy is suspected, during treatment with doxorubicin [see Warnings and Precautions (5.8) and Use in Specific Populations (8.6)].
- Doxorubicin may induce chromosomal damage in sperm, which may lead to loss of fertility and offspring with birth defects. Advise patients to use effective contraception during and for 6 months after treatment [see Warnings and Precautions (5.8) and Use in Specific Populations (8.6)].
- Doxorubicin can cause premature menopause in females and loss of fertility in males [see Use in Specific Populations (8.6)].
- Discontinue nursing while receiving doxorubicin [see Use in Specific Populations (8.3)].
- Doxorubicin can cause nausea, vomiting, diarrhea, mouth/oral pain and sores. Advise patients to contact a healthcare provider should they develop any severe symptoms that prevent them from eating and drinking [see Adverse Reactions (6)].
- Doxorubicin causes alopecia [see Adverse Reactions (6.1)].
- Doxorubicin can cause their urine to appear red for 1 to 2 days after administration.

Manufactured by

THYMOORGAN PHARMAZIE GmbH

Schiffgraben 23, 38690 Goslar, Germany

Distributed by

Hikma Pharmaceuticals USA Inc.

Berkeley Heights, NJ 07922

Revised March 2021

127.207.045/00

Patient Information

DOXORUBICIN (dok-suh-roo-buh-sin) HYDROCHLORIDE for Injection, for intravenous use

What is the most important information I should know about Doxorubicin?

Doxorubicin may cause serious side effects including:

- Heart failure. Doxorubicin may cause heart muscle damage that may lead to heart failure, which is a condition in which the heart does not pump well. Heart failure is irreversible in some cases and can lead to death. Heart failure can happen during your treatment with Doxorubicin or months to years after stopping treatment. Your risk of heart muscle damage increases with higher total amounts of doxorubicin hydrochloride that you receive in your lifetime. Your risk of heart failure is higher if you:
  - already have other heart problems
  - have had or are currently receiving radiation therapy to your chest
  - have had treatment with certain other anti-cancer medicines
  - take other medicines that can have severe side effects on your heart

Tell your doctor if you get any of these symptoms of heart failure during or after treatment with Doxorubicin:

- extreme tiredness or
- fast heartbeat weakness
- swelling of your feet and ankles
- shortness of breath

Your doctor will do tests to check the strength of your heart muscle before, during, and after your treatment with Doxorubicin.

- Risk of new cancers. You may have an increased risk of developing certain blood cancers called acute myelogenous leukemia (AML) or myelodysplastic syndrome (MDS) after treatment with doxorubicin. Talk with your doctor about your risk of developing new cancers if you take Doxorubicin.
- Skin damage near the vein where Doxorubicin is given (Injection site reaction). Doxorubicin can damage the skin if it leaks out of the vein. Symptoms of infusion reaction include blisters and skin sores at injection site which may require skin grafts.
- Decreased blood cell counts. Doxorubicin can cause a decrease in neutrophils (a type of white blood cells important in fighting bacterial infections) and platelets (important for clotting and to control bleeding). This may lead to a serious infection, the need for blood transfusions, treatment in a hospital and death. Your doctor will check your blood cell count during your treatment with Doxorubicin and after you have stopped your treatment. Call your doctor right away if you get a fever (temperature of 100.4°F or greater) or chills with shivering.

What is Doxorubicin?

Doxorubicin is a prescription medicine used to treat certain types of cancers. Doxorubicin may be used alone or along with other anti-cancer medicines.

Who should not receive Doxorubicin?

Do not receive Doxorubicin if:

- you have had a recent heart attack or have severe heart problems
- your blood cell counts (platelets, red blood cells, and white blood cells) are very low because of prior chemotherapy
- you have a severe liver problem
- you have had a serious allergic reaction to doxorubicin hydrochloride

What should I tell my doctor before receiving Doxorubicin?

Before you receive Doxorubicin, tell your doctor if you:

- have heart problems including heart failure
- are currently receiving radiation therapy or plan to receive radiation to the chest
- have severe liver problems
- have had an allergic reaction to doxorubicin
- have any other medical conditions
- are pregnant or plan to become pregnant. Doxorubicin can harm your unborn baby. Women who are able to become pregnant and men who take Doxorubicin should use effective birth control (contraception) during treatment and for 6 months after treatment. Talk to your doctor about birth control methods. If you or your partner becomes pregnant, tell your doctor right away.
- are breastfeeding or plan to breast feed. Doxorubicin can pass into your breast milk and harm your baby. You and your doctor should decide if you will receive Doxorubicin or breastfeed. You should not do both.

Tell your doctor about all the medicines you take, including prescription and over-the-counter medicines, vitamins, and herbal supplements. Doxorubicin can interact with other medicines. Do not start any new medicine before you talk with the doctor that prescribed Doxorubicin.

Know the medicines you take. Keep a list to show your doctor and pharmacist each time you get a new medicine.

How will I receive Doxorubicin?

- Doxorubicin will be given to you into your vein.

What are the possible side effects of Doxorubicin?

Doxorubicin may cause serious side effects, including:

- See “What is the most important information I should know about Doxorubicin?”

Doxorubicin may cause lower sperm counts and sperm problems in men.

This could affect your ability to father a child and cause birth defects. Talk to your healthcare provider if this is a concern for you. Talk to your healthcare provider about family planning options that might be right for you.

Irreversible amenorrhea or early menopause. Your periods (menstrual cycle) may completely stop when you receive Doxorubicin. Your periods may or may not return following treatment. Talk to your healthcare provider about family planning options that might be right for you.

The most common side effects of Doxorubicin include:

- Total hair loss (alopecia). Your hair may re-grow after your treatment
- nausea
- vomiting

Other side effects:

- Red colored urine. You may have red colored urine for 1 to 2 days after your infusion of Doxorubicin. This is normal. Tell your doctor if it does not stop in a few days, or if you see what looks like blood or blood clots in your urine.
- Darkening of your nails or separation of your nails from your nail bed.
- Easy bruising or bleeding.
- Call your doctor if you have severe symptoms that prevent you from eating or drinking, such as:
  - nausea
  - vomiting
  - diarrhea
  - mouth sores

Tell your doctor or nurse if you have any side effect that bothers you or that does not go away.

These are not all of the possible side effects of Doxorubicin.

Call your doctor for medical advice about side effects. You may report side effects to FDA at 1-800-FDA-1088.

General information about the safe and effective use of Doxorubicin.

Medicines are sometimes prescribed for purposes other than those listed in a Patient Information leaflet.

You can ask your pharmacist or doctor for information about Doxorubicin that is written for health professionals.

For more information, call 1-877-845-0689.

What are the ingredients of Doxorubicin?

Active ingredient: doxorubicin hydrochloride

Inactive ingredients for Doxorubicin Hydrochloride for Injection: Lactose Monohydrate.

This Patient Information has been approved by the U.S. Food and Drug Administration.

Manufactured by

THYMOORGAN PHARMAZIE GmbH

Schiffgraben 23, 38690 Goslar, Germany

Distributed by

Hikma Pharmaceuticals USA Inc.

Berkeley Heights, NJ 07922

Revised March 2021

127.207.045/00

10 MG PACKAGE/LABEL PRINCIPAL DISPLAY PANEL

NDC 0143-9092-01 Rx only
DOXOrubicin
HCl for Injection, USP
10 mg per vial
For Intravenous use ONLY
LYOPHILIZED

50 MG PACKAGE/LABEL PRINCIPAL DISPLAY PANEL

NDC 0143-9093-01 Rx only
DOXOrubicin
HCl for Injection, USP
50 mg per vial
For Intravenous use ONLY
LYOPHILIZED